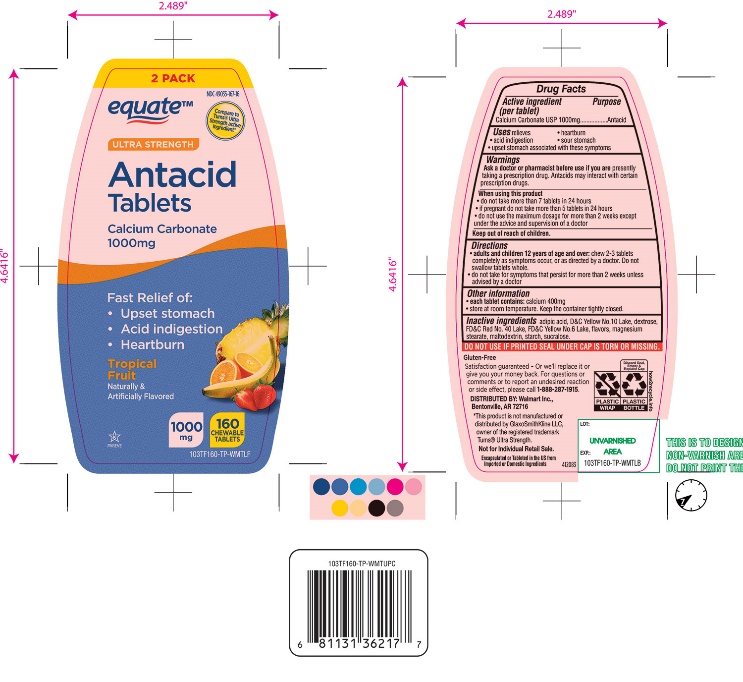 DRUG LABEL: Ultra Strength

NDC: 49035-167 | Form: TABLET, CHEWABLE
Manufacturer: Wal-Mart Stores,Inc.,
Category: otc | Type: HUMAN OTC DRUG LABEL
Date: 20251027

ACTIVE INGREDIENTS: CALCIUM CARBONATE 1000 mg/1 1
INACTIVE INGREDIENTS: ADIPIC ACID; D&C YELLOW NO. 10; DEXTROSE, UNSPECIFIED FORM; FD&C RED NO. 40; FD&C YELLOW NO. 6; MAGNESIUM STEARATE; MALTODEXTRIN; STARCH, CORN; SUCRALOSE

Ultra Strength Twin Pack Chewable Tablets

Active ingredient (per tablet)

Calcium Carbonate USP 1000mg

Purpose

Antacid

Uses

relieves

- heartburn
- acid indigestion
- sour stomach
- upset stomach associated with these symptoms

Warnings

Ask a doctor or pharmacist before use if you arepresently taking a prescription drug. Antacids may interact with certain prescription drugs.

When using this product

- do not take more than 7 tablets in 24 hours
- if pregnant do not take more than 5 tablets in 24 hours
- do not use the maximum dosage for more than 2 weeks except under the advice and supervision of a doctor.

Directions

- adults and children 12 years of age and over:chew 2-3 tablets completely as symptoms occur, or as directed by a doctor. Do not swallow tablets whole.
- do not take for symptoms that persist for more than 2 weeks unless advised by a doctor.

Other information

- each tablet contains:calcium 400mg
- store at room temperature. Keep the container tightly closed.

Inactive ingredients

adipic acid, D&C Yellow No. 10 Lake, dextrose, FD&C Red No. 40 Lake, FD&C Yellow No. 6 Lake, flavors, magnesium stearate, maltodextrin, starch, sucralose.

Questions?

1-866-467-2748

SAFETY SEALED: DO NOT USE IF PRINTED SEAL UNDER CAP IS TORN OR MISSING.

Package/Label Principal Display Panel

NDC 49035-167-16

*Compare to the active ingredient in Ultra Strength Tums®

ULTRA STRENGTH

Antacid Tablets

Calcium Carbonate 1000 mg

Fast Relief of Upset Stomach, Heartburn and Acid Indigestion.

Tropical Fruit

Naturally and Artificially Flavored

160 CHEWABLE TABLETS

GLUTEN- FREE

Satisfaction guaranteed- Or we will replace it or give you your money back. For questions or to report an undesired reaction or side effect, please call 1-888-287-1915.

Encapsulated or Tableted in the US from Imported or Domestic Ingredients.

Distributed by: Wal-Mart Stores, Inc.,

Bentonville, AR 72716

*This product is not manufactured or distributed by GlaxoSmithKline LLC, owner of the registered trademark, Ultra Strength Tums®.

Not for individual Retail Sale.

Encapsulated or Tableted in the US from Imported or Domestic Ingredients